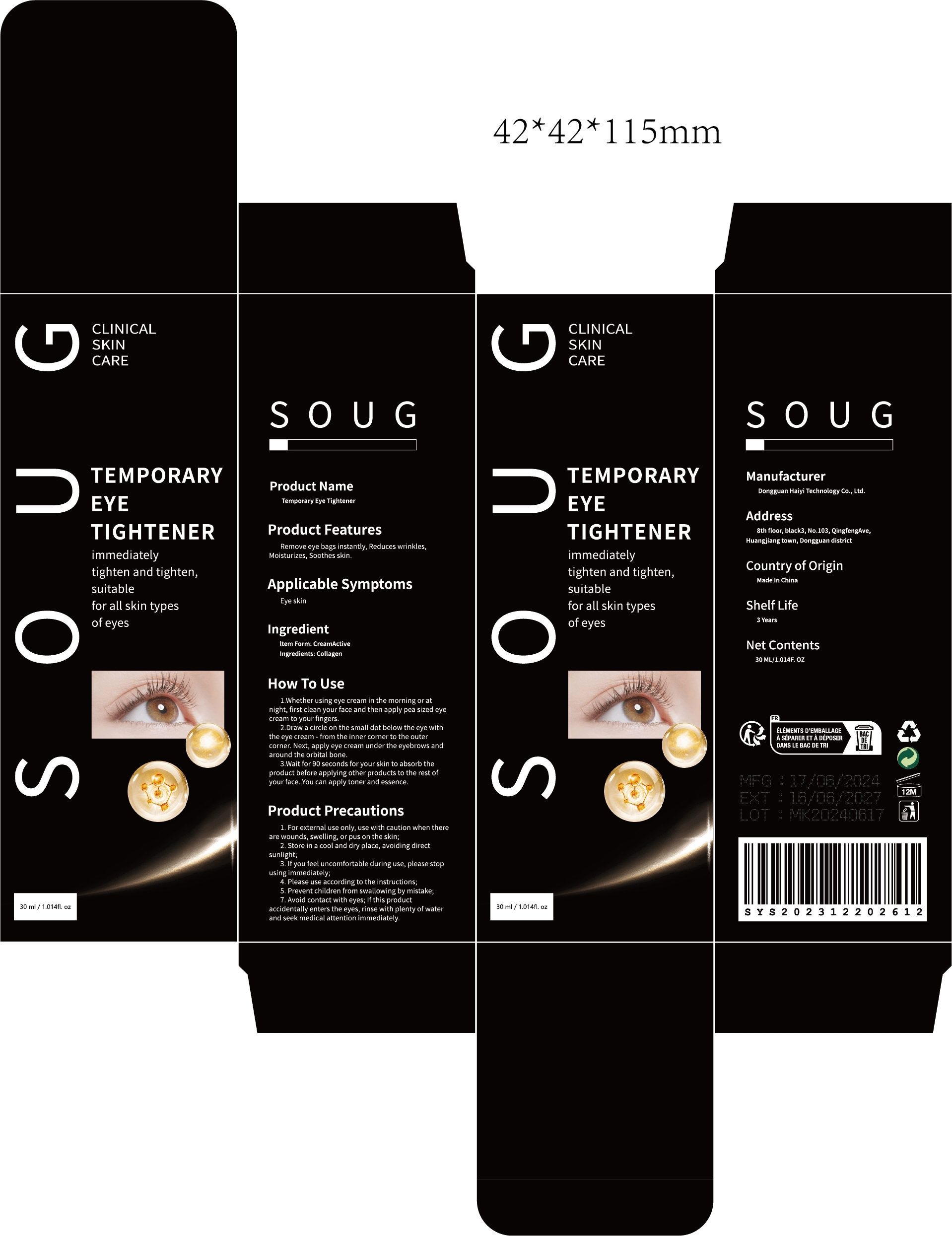 DRUG LABEL: Temporary Eye Tightener
NDC: 84732-005 | Form: CREAM
Manufacturer: Dongguan Haiyi Technology Co.,Ltd.
Category: otc | Type: HUMAN OTC DRUG LABEL
Date: 20240923

ACTIVE INGREDIENTS: EQUINE COLLAGEN 1 mg/30 mL
INACTIVE INGREDIENTS: WATER

Active ingredient

Collagen

Inactive ingredient

water

Purpose section

Remove eye bags instantly, Reduces wrinkles Moisturizes, Soothes skin.

Warning

1. For external use only, use with caution when thereare wounds, swelling, or pus on the skin;

2. Store in a cool and dry place, avoiding directsunlight;

3. lf you feel uncomfortable during use, please stopusingimmediately;

4. Please use according to the instructions;

5.Prevent children from swallowing by mistake,

7.Avoid contact with eyes; lfthis productaccidentally enters the eyes, rinse with plenty of waterand seek medical attention immediately

stop use

lf you feel uncomfortable during use, please stop using immediately;

not use

Not suitable for use by children, pregnantor breast feeding people.

OUT OF CHILDREN

KEEP THE PRODUCT OUT OF REACH OF CHILDREN to

HOW TO USE

1.Whether using eye cream in the morning or atnight, first clean your face and then apply pea sized eyecream to your fingers.
2.Draw a circle on the small dot below the eye withthe eye cream - from the inner corner to the outercorner. Next, apply eye cream under the eyebrows andaround the orbital bone.

3.Wait for 90 seconds for your skin to absorb theproduct before applying other products to the rest ofyour face. You can apply toner and essence.

Dosage

take an appropriateamount,Use 2-3 times a week